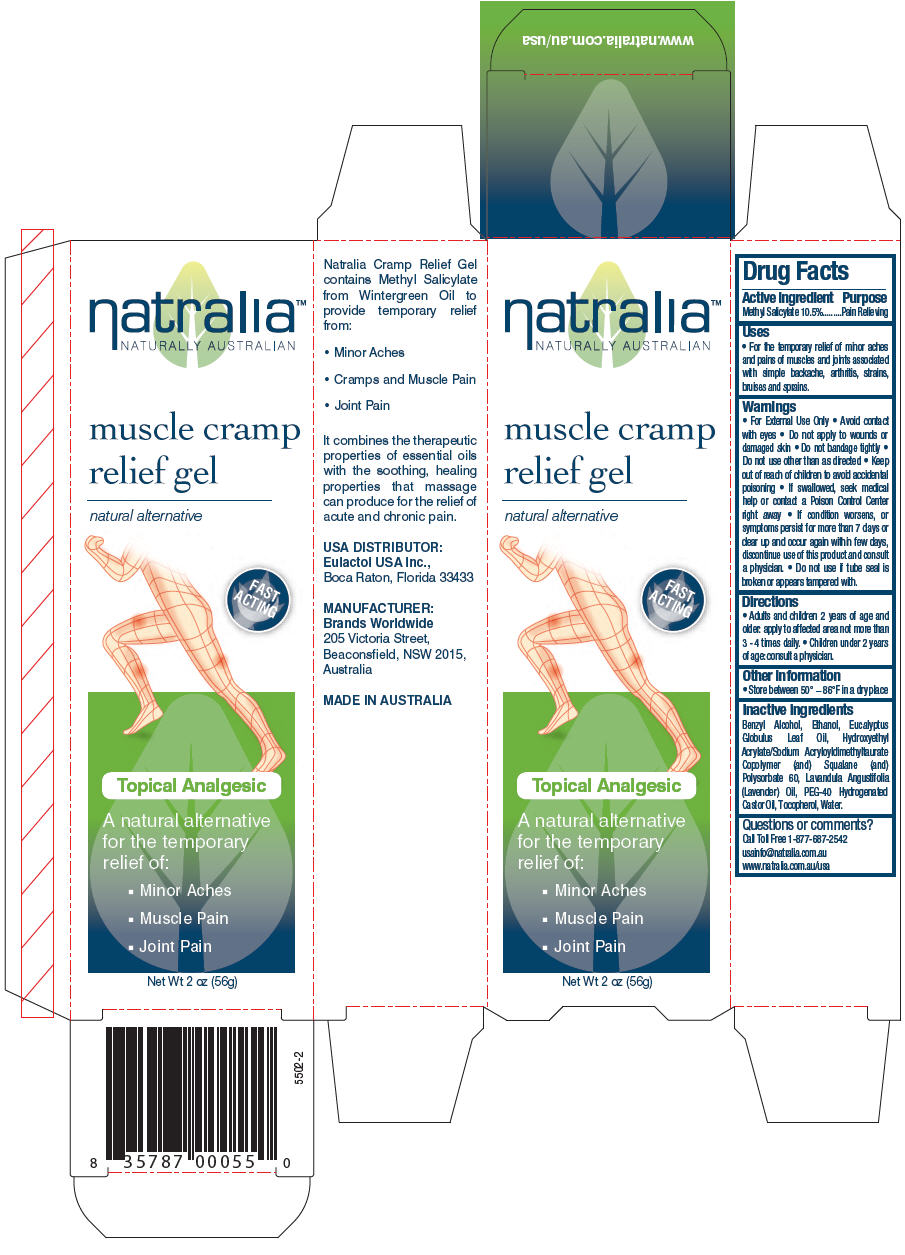 DRUG LABEL: Natralia Cramp Relief
NDC: 43251-3213 | Form: GEL
Manufacturer: Laderma Trading Pty Ltd
Category: otc | Type: HUMAN OTC DRUG LABEL
Date: 20110118

ACTIVE INGREDIENTS: Methyl Salicylate 105 mg/1 g
INACTIVE INGREDIENTS: Benzyl Alcohol; Alcohol; Corymbia Citriodora Leaf Oil; Squalane; Polysorbate 60; Lavender Oil; Polyoxyl 40 Hydrogenated Castor Oil; Alpha-Tocopherol; Water

natralia™
NATURALLY AUSTRALIAN
muscle cramp
relief gel

Drug Facts

Active ingredient

Methyl Salicylate 10.5%

Purpose

Pain Relieving

Uses

- For the temporary relief of minor aches and pains of muscles and joints associated with simple backache, arthritis, strains, bruises and sprains.

Warnings

WHEN USING

- For External Use Only
- Avoid contact with eyes
- Do not apply to wounds or damaged skin
- Do not bandage tightly
- Do not use other than as directed

- Keep out of reach of children to avoid accidental poisoning
- If swallowed, seek medical help or contact a Poison Control Center right away

STOP USE

- If condition worsens, or symptoms persist for more than 7 days or clear up and occur again within few days, discontinue use of this product and consult a physician.

- Do not use if tube seal is broken or appears tampered with.

Directions

- Adults and children 2 years of age and older: apply to affected area not more than 3 - 4 times daily.
- Children under 2 years of age: consult a physician.

Other information

- Store between 50° – 86°F in a dry place

Inactive ingredients

Benzyl Alcohol, Ethanol, Eucalyptus Globulus Leaf Oil, Hydroxyethyl Acrylate/Sodium Acryloyldimethyltaurate Copolymer (and) Squalane (and) Polysorbate 60, Lavandula Angustifolia (Lavender) Oil, PEG-40 Hydrogenated Castor Oil, Tocopherol, Water.

Questions or comments?

Call Toll Free 1-877-687-2542

usainfo@natralia.com.au

www.natralia.com.au/usa

PRINCIPAL DISPLAY PANEL - 56g Tube Carton

natralia™
NATURALLY AUSTRALIAN

muscle cramp
relief gel

natural alternative

FAST
ACTING

Topical Analgesic

A natural alternative
for the temporary
relief of:

- Minor Aches
- Muscle Pain
- Joint Pain

Net Wt 2 oz (56g)